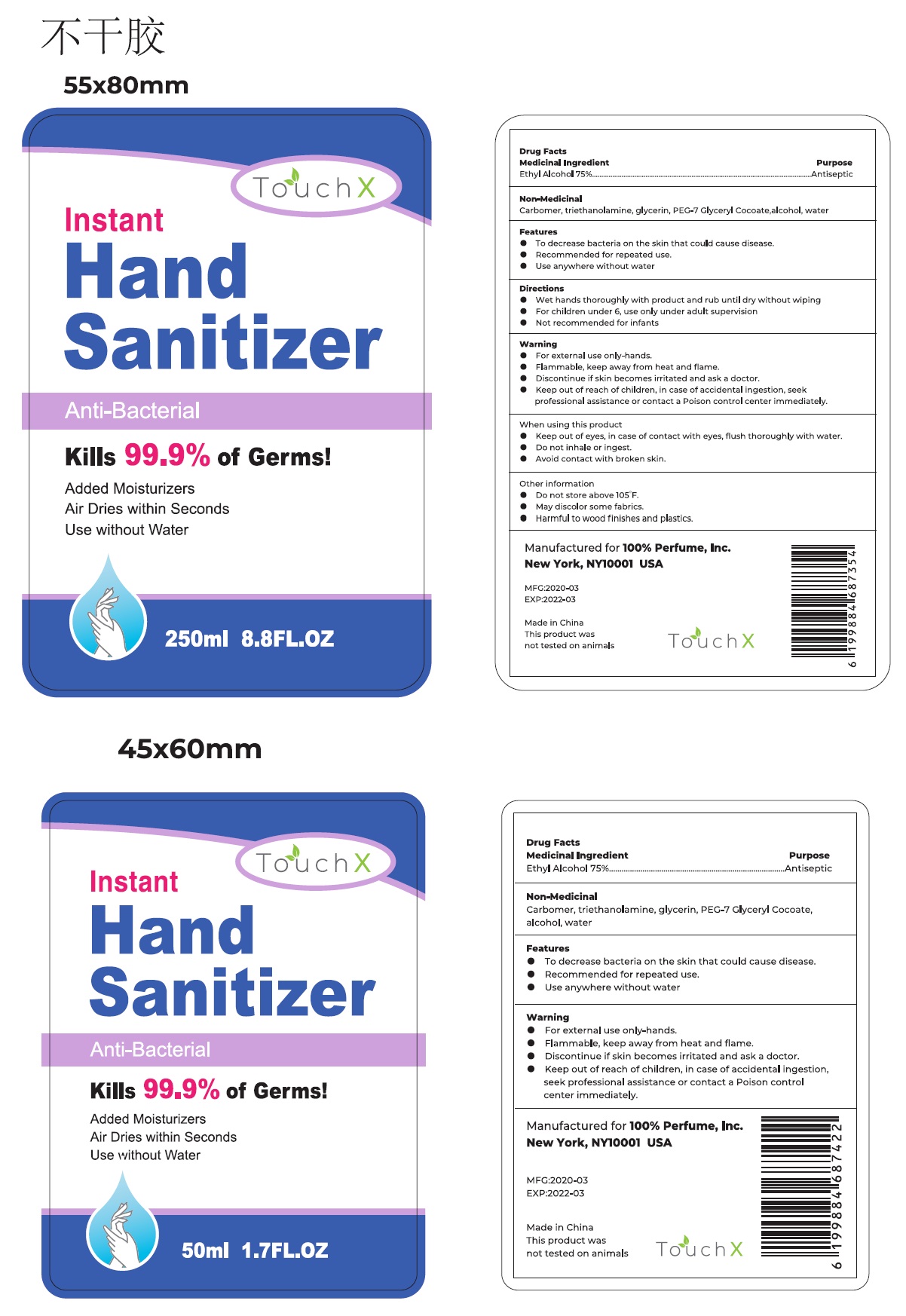 DRUG LABEL: TOUCHX INSTANT HAND SANITIZER
NDC: 74875-100 | Form: GEL
Manufacturer: Yiwu Story of Love Cosmetic Co., Ltd.
Category: otc | Type: HUMAN OTC DRUG LABEL
Date: 20200415

ACTIVE INGREDIENTS: ALCOHOL 75 mL/100 mL
INACTIVE INGREDIENTS: CARBOMER HOMOPOLYMER, UNSPECIFIED TYPE; TROLAMINE; GLYCERIN; PEG-7 GLYCERYL COCOATE; WATER

TouchX Instant Hand Sanitizer

Medicinal Ingredient

Ethyl Alcohol 75%

Purpose

Antiseptic

Features

- To decrease bacteria on the skin that could cause disease.
- Recommended for repeated use
- Use anywhere without water

Warning

- For external use only-hands
- Flammable, keep away from heat and flame.
- Discontinue if skin becomes irritated and ask a doctor

When using this product

- Keep out of eyes, in case of contact with eyes, flush thoroughly with water
- Do not inhale or ingest
- Avoid contact with broken skin

- Keep out of reach of children, in case of accidental ingestion, seek professional assistance or contact a Poison control center immediately.

Directions

- Wet hands thoroughly with product and rub until dry without wiping
- For children under 6, use only under adult supervision
- Not recommended for infants

Other information

- Do not store above 105 F.
- May discolor some fabrics.
- Harmful to wood finishes and plastics.

Non-Medicinal

Carbomer, triethanolamine, glycerin, PEG-7 Glyceryl Cocoate, alcohol, water

Anti-Bacterial

Kills 99.9% of Germs!

Added Moisturizers

Air Dries within Seconds

Use without Water

Manufactured for 100% Perfume, Inc.

New York, NY10001 USA

Made in China

This product was not tested on animals